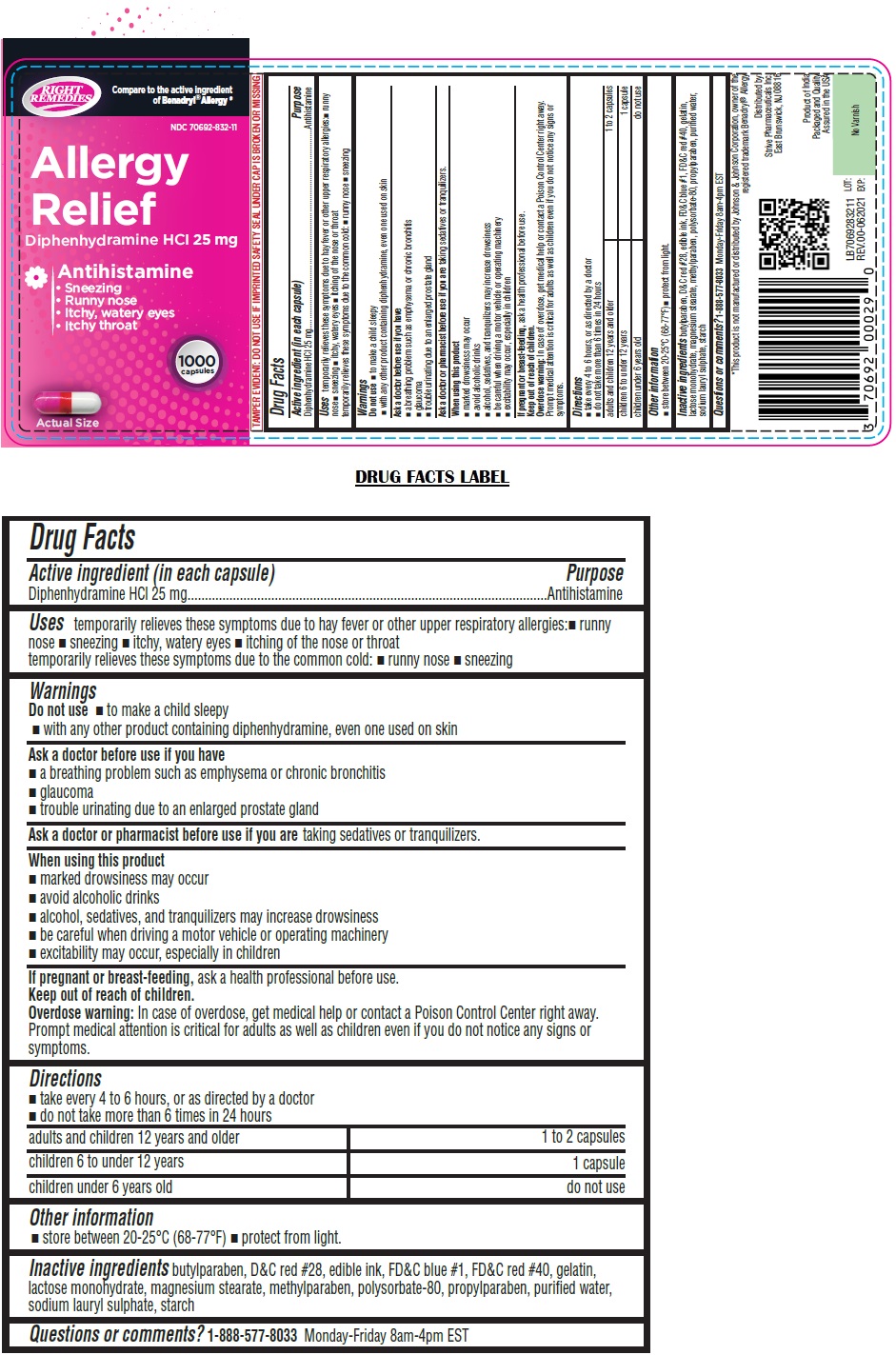 DRUG LABEL: RIGHT REMEDIES Allergy Relief
NDC: 70692-832 | Form: CAPSULE
Manufacturer: Strive Pharmaceuticals Inc
Category: otc | Type: HUMAN OTC DRUG LABEL
Date: 20241211

ACTIVE INGREDIENTS: DIPHENHYDRAMINE HYDROCHLORIDE 25 mg/1 1
INACTIVE INGREDIENTS: BUTYLPARABEN; D&C RED NO. 28; FD&C BLUE NO. 1; FD&C RED NO. 40; GELATIN, UNSPECIFIED; LACTOSE MONOHYDRATE; MAGNESIUM STEARATE; METHYLPARABEN; POLYSORBATE 80; PROPYLPARABEN; WATER; SODIUM LAURYL SULFATE; STARCH, CORN

RIGHT REMEDIES Allergy Relief

Active ingredient (in each capsule)

Diphenhydramine HCl 25 mg

Purpose

Antihistamine

Uses

temporarily relieves these symptoms due to hay fever or other upper respiratory allergies: • runny nose • sneezing • itchy, watery eyes • itching of the nose or throat
temporarily relieves these symptoms due to the common cold: • runny nose • sneezing

Warnings

Do not use • to make a child sleepy
• with any other product containing diphenhydramine, even one used on skin

Ask a doctor before use if you have
• a breathing problem such as emphysema or chronic bronchitis
• glaucoma
• trouble urinating due to an enlarged prostate gland

Ask a doctor or pharmacist before use if you are taking sedatives or tranquilizers.

When using this product
• marked drowsiness may occur
• avoid alcoholic drinks
• alcohol, sedatives, and tranquilizers may increase drowsiness
• be careful when driving a motor vehicle or operating machinery
• excitability may occur, especially in children

If pregnant or breast-feeding, ask a health professional before use.

Keep out of reach of children.
Overdose warning: In case of overdose, get medical help or contact a Poison Control Center right away. Prompt medical attention is critical for adults as well as children even if you do not notice any signs or symptoms.

Directions

• take every 4 to 6 hours, or as directed by a doctor
• do not take more than 6 times in 24 hours

adults and children 12 years and older | 1 to 2 capsules
children 6 to under 12 years | 1 capsule
children under 6 years old | do not use

Other information

• store between 20-25°C (68-77°F) • protect from light.

Inactive ingredients

butylparaben, D&C red #28, edible ink, FD&C blue #1, FD&C red #40, gelatin, lactose monohydrate, magnesium stearate, methylparaben, polysorbate-80, propylparaben, purified water, sodium lauryl sulphate, starch

Questions or comments?

1-888-577-8033 Monday-Friday 8am-4pm EST

Compare to the active ingredient of Benadryl®Allergy*

• Sneezing
• Runny nose
• Itchy, watery eyes
• Itchy throat

TAMPER EVIDENT: DO NOT USE IF IMPRINTED SAFETY SEAL UNDER CAP IS BROKEN OR MISSING

*This product is not manufactured or distributed by Johnson & Johnson Corporation, owner of the registered trademark Benadryl® Allergy

Distributed by:
Strive Pharmaceuticals Inc.
East Brunswick, NJ 08816

Product of India
Packaged and Quality Assured in the USA